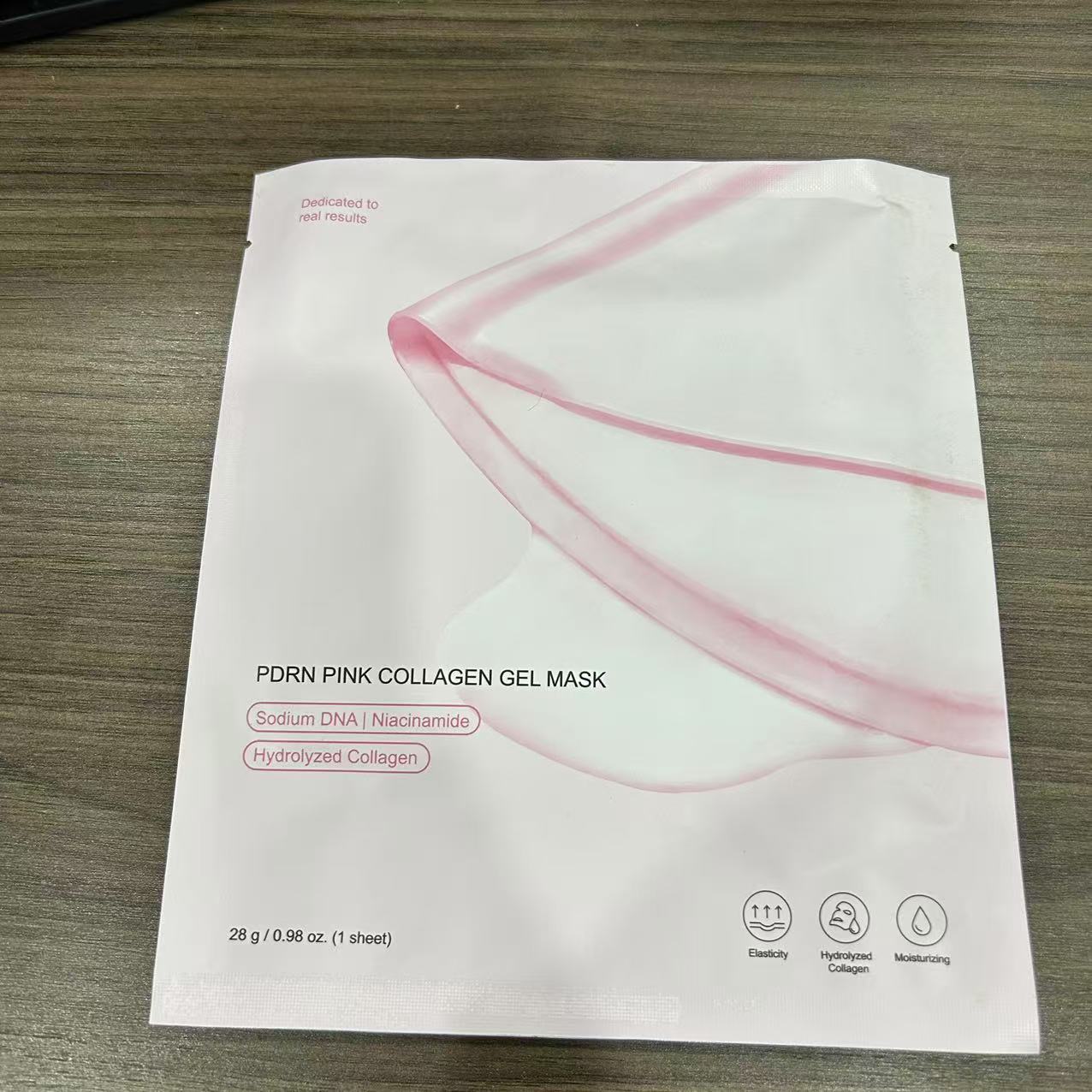 DRUG LABEL: PDRN PINK COLLAGEN MASK
NDC: 84766-0005 | Form: GEL
Manufacturer: COMFMET LIMITED
Category: otc | Type: HUMAN OTC DRUG LABEL
Date: 20241023

ACTIVE INGREDIENTS: NIACINAMIDE 0.3 g/100 g; GLUCOMANNAN 1 g/100 g
INACTIVE INGREDIENTS: SODIUM LAURETH SULFATE; PHENOXYETHANOL; 2,3-DIHYDROXY BENZOIC ACID; 1,2-HEXANEDIOL; POTASSIUM CITRATE; CITRIC ACID; POLYURETHANE-35 (NOT MORE THAN 1000 MPA.S AT 40%); P-HYDROXYBENZOATE ANION; WATER; .ALPHA.-BUTYLDIMETHYLSILYL-AND .OMEGA.-3-METHACRYLOXYPROPYLDIMETHYLSILYL-TERMINATED POLYDIMETHYLSILOXANE (1000 MW); COLLAGEN, SOLUBLE, FISH SKIN; ALLANTOIN PANTHENOL; 2-OCTANOL; CARRAGEENAN SODIUM; 2-HYDROXYACETOPHENONE; GLYCERIN; AGARICIC ACID

ACTIVE INGREDIENT

Niacinamide......0.3%

Glucomannan......1%

PURPOSE

Skin protectant

INDICATIONS AND USAGE

1. After cleansing,smooth out the skin texture using toner.
2. Open the pouch and remove the film from the upper and lower masks and place the upper mask centered around the eyes and the lower mask centered around the mouth
3. Remove the mask sheets after about 1-3 hours when the sheet turns transparent
4.Gently pat the remaining serum on the skin for absorption.The time it takes for the mask sheets to become transparent may vary for each individual.

WARNINGS

Warnings: For external use only. Avoid contact with eyes. Not for human consumption. Discontinue use if irritation occurs. If irritation persists, consult a physician. Use immediately after opening. Caution: Store in cool and dry place. Use Immediately after opening.

Do not use on areas with wounds, eczema, or dermatitis.

When using this product, keep out of eyes. If eye contact occurs, rinse well with water.

STOP USE

When the skin hurts

Stop use and ask a doctor if you have

a. Redness, swelling, itchiness, irritation, or other similar symptoms.
b. Occurrence of the above symptoms upon exposure to direct sunlight.

Keep out of reach of children. If product is swallowed, get medical help or contact a poison control center right away.

INDICATIONS AND USAGE

Protects, restores and soothes the skin
Softens, smoothens, enhances radiance and brightens skin

INACTIVE INGREDIENT

water

glycerin

polyurethane-35

Carageenan sodium

p-hydroxyacetoph-enone

1,2-hexanediol

agar

Potassium Citrate

hydrolyzed collagen

hydroxybenzoate

allantoin

PEG-12 polydimethylsiloxane

citric acid

Cl 12490

sodium laureth sulfate

2-phenoxyethanol

octanol

benzoic acid

QUESTIONS

Email:commet515@gmail.com

DOSAGE AND ADMINISTRATION

After cleansing, Open the pouch and remove the film from the upper and lower masks and place the upper mask centered around the eyes and the lower mask centered around the mouth，Remove the mask sheets after about 1-3 hours when the sheet turns transparent